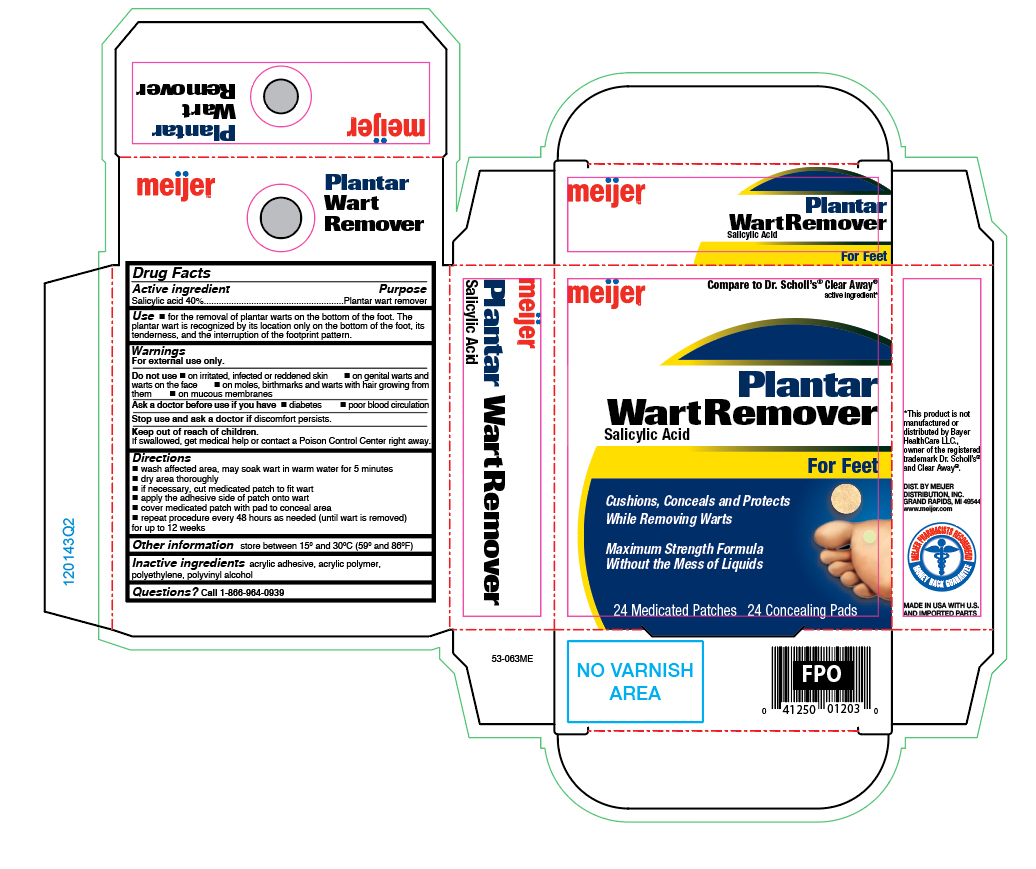 DRUG LABEL: Salicylic Acid
NDC: 41250-243 | Form: PATCH
Manufacturer: Meijer Distribution Inc
Category: otc | Type: HUMAN OTC DRUG LABEL
Date: 20260120

ACTIVE INGREDIENTS: SALICYLIC ACID 40 mg/24 1
INACTIVE INGREDIENTS: POLYVINYL ALCOHOL, UNSPECIFIED; VINYL ACETATE; HIGH DENSITY POLYETHYLENE

Meijer Medicated Plantar Wart Remover

Active ingredient

Salicylic acid 40%w/w

Purpose

Plantar wart remover

Uses

- for the removal of plantar warts on the bottom of the foot. The plantar wart is recognized by its location only on the bottom of the foot, its tenderness, and the interruption of the footprint pattern.

Warnings

For external use only.

Do not use

- if you are diabetic or have poor blood circulation, except under the advise and supervision of a doctor or podiatrist
- on irritated, infected or reddened skin
- on genital warts and warts on the face
- on moles, birthmarks and warts with hair growing from them
- on mucous membranes

Keep this and all drugs out of the reach of children.

If swallowed, get medical help or contact a Poison Control Center right away.

If discomfort persists

see your doctor or podiatrist.

Directions

- wash affected area, may soak wart in warm water for 5 minutes
- dry area thoroughly
- if necessary, cut medicated patches to fit wart
- apply the adhesive side of patch onto wart
- cover patch with pads to conceal area
- repeat procedure every 48 hours as needed (until wart is removed) for up to 12 weeks

Other information

store between 59° and 86°F (15° and 30°C)

Inactive ingredients

acrylic adhesive, acrylic polymer, polyethylene, polyvinyl alcohol

Questions?

call 1-866-964-0939

Principal Display Panel

meijer

Plantar Wart Remover

Salicylic Acid

For feet

- Cushions, Conceals and Protects while removing warts
- Maximum Strength Formula without the mess of liquids

24 Medicated Patches 24 Concealing Pads